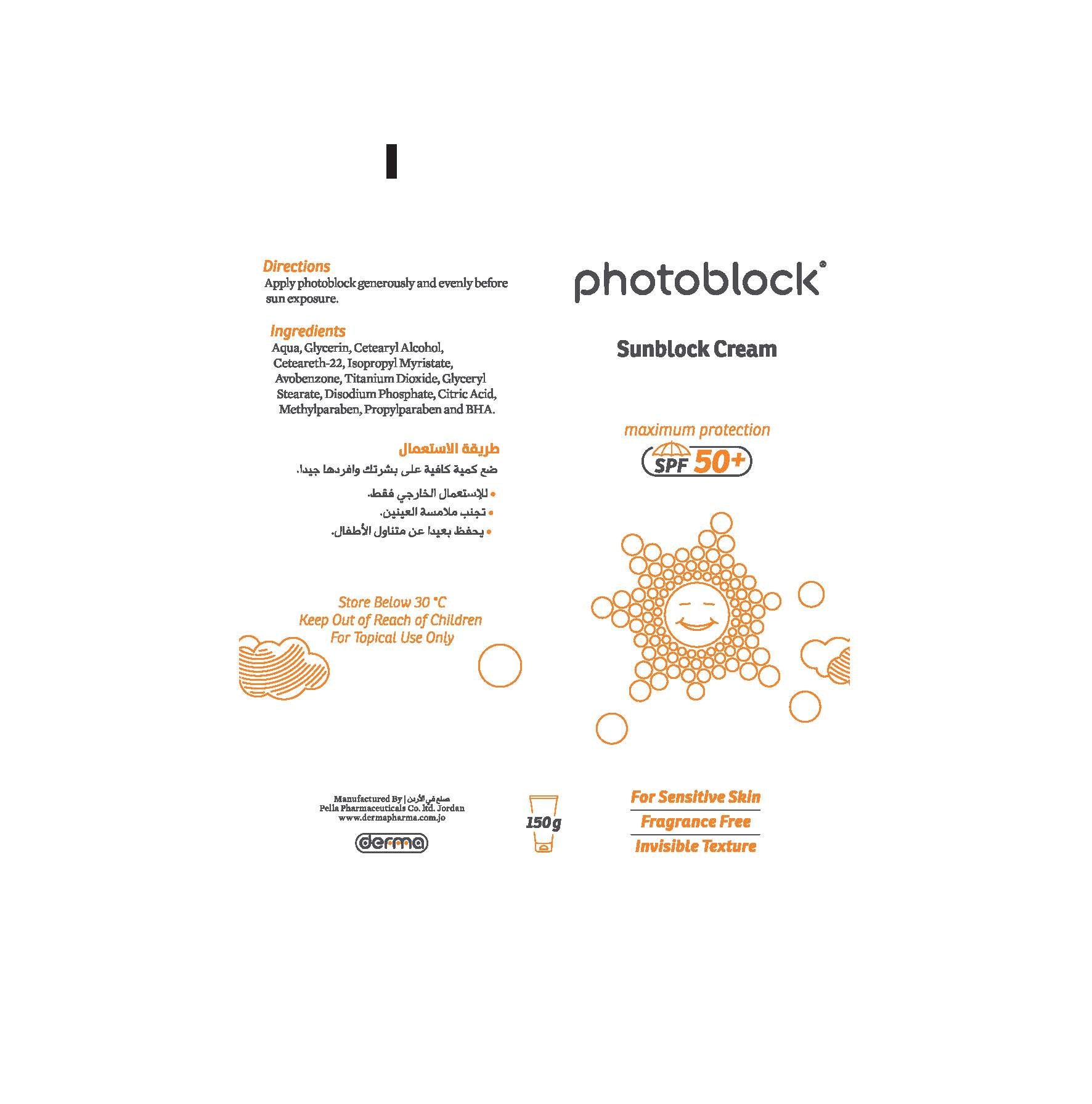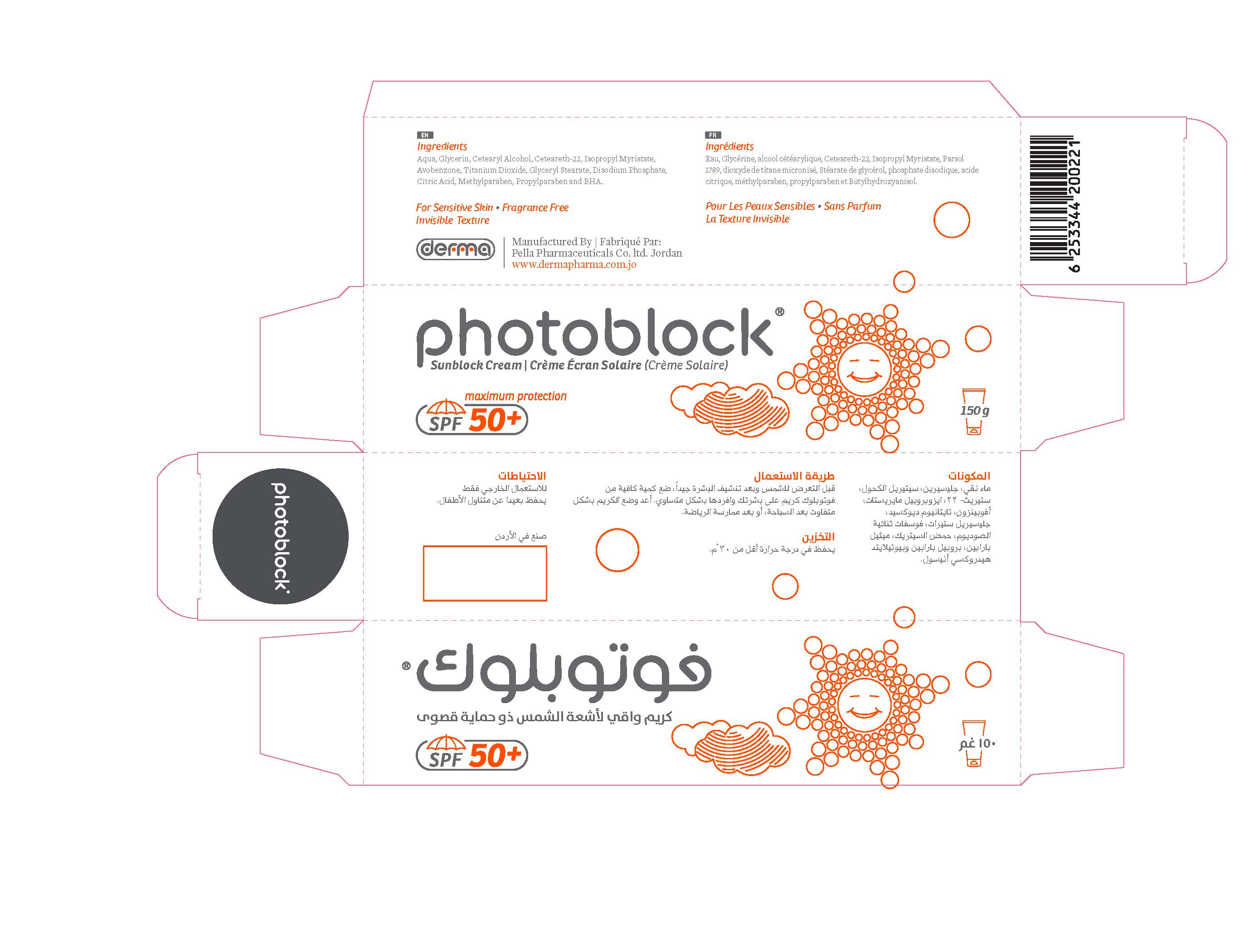 DRUG LABEL: Photoblock
NDC: 82160-221 | Form: CREAM
Manufacturer: Pella Pharmaceuticals Co. Ltd
Category: otc | Type: HUMAN OTC DRUG LABEL
Date: 20211124

ACTIVE INGREDIENTS: TITANIUM DIOXIDE 45 mg/150 g; AVOBENZONE 45 mg/150 g
INACTIVE INGREDIENTS: BUTYLATED HYDROXYANISOLE; CETEARETH-22; ISOPROPYL MYRISTATE; GLYCERYL MONOSTEARATE; ANHYDROUS CITRIC ACID; WATER; GLYCERIN; CETOSTEARYL ALCOHOL; METHYLPARABEN; PROPYLPARABEN; SODIUM PHOSPHATE, DIBASIC

Photoblock

Forms and Presentation

Cream: Tube of 150 g.

Active Ingredients

Avobenzone

Titanium Dioxide

Inactive Ingredients

Aqua, Glycerin, Cetearyl Alcohol, Ceteareth-22, lsopropyl Myristate, Glyceryl Stearate, Disodium Phosphate, Citric Acid, Methylparaben, Propylparaben and BHA.

Purpose

Sunscreen

Properties

Photoblock® Cream is a sunscreen that is characterized by its maximum protection.
Photoblock® cream doesn't cause acne and doesn't clog the skin pores. Photoblock® SPF 50+ Cream protects against UV A and UVB, it suits the whole family members.

Indications

Photoblock® cream is used to provide maximum protection as well as youth and freshness.
It contains Titanium Dioxide which is well known as a physical sunscreen that protects against UVB and sun burns, in addition to Avobenzone which provides complete protection against UVA.

Contraindications

Hypersensitivity to any of the components

Precautions

Keep out of reach of children

Warnings

- For external use only
- Avoid contact with eyes

Side effects

Photoblock® Cream has no side effects, its use is harmless.
Preferably used by small children under the supervision of an adult.

Dosage and administration

Before sun exposure, apply a sufficient quantity on skin and massage gently.
Reapply every 2 hours or after swimming or sports.

Storage conditions

Store at a temperature below 30 ° C.